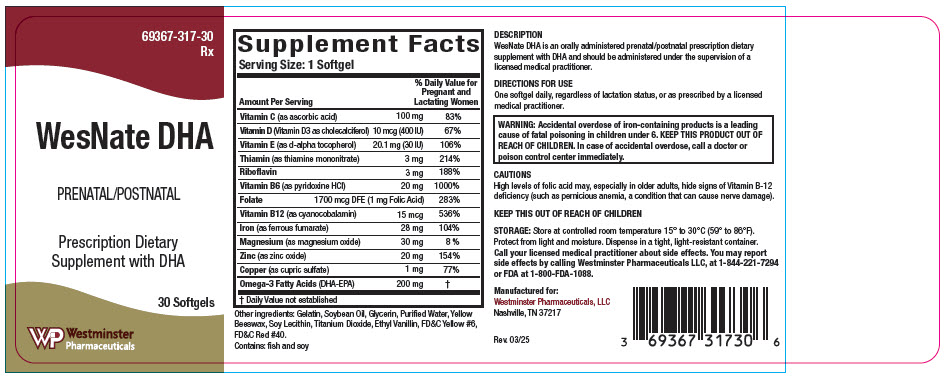 DRUG LABEL: WesNate DHA
NDC: 69367-317 | Form: CAPSULE, GELATIN COATED
Manufacturer: Westminster Pharmaceuticals, LLC
Category: other | Type: DIETARY SUPPLEMENT
Date: 20250709

ACTIVE INGREDIENTS: ASCORBIC ACID 100 mg/1 1; CHOLECALCIFEROL 400 [iU]/1 1; .ALPHA.-TOCOPHEROL, D- 30 [iU]/1 1; THIAMINE MONONITRATE 3 mg/1 1; RIBOFLAVIN 3 mg/1 1; PYRIDOXINE HYDROCHLORIDE 20 mg/1 1; FOLIC ACID 1 mg/1 1; CYANOCOBALAMIN 15 ug/1 1; FERROUS FUMARATE 28 mg/1 1; MAGNESIUM OXIDE 30 mg/1 1; ZINC OXIDE 20 mg/1 1; CUPRIC SULFATE 1 mg/1 1; OMEGA-3 FATTY ACIDS 200 mg/1 1
INACTIVE INGREDIENTS: GELATIN, UNSPECIFIED; GLYCERIN; SOYBEAN OIL; YELLOW WAX; WATER; SOYBEAN LECITHIN; TITANIUM DIOXIDE; ETHYL VANILLIN; FD&C YELLOW NO. 6; FD&C RED NO. 40

WesNate DHA

HEALTH CLAIM

Prenatal/Postnatal Prescription Dietary Supplement

69367-317-30
Rx

DESCRIPTION

WesNate DHA is an orally administered prenatal/postnatal prescription dietary supplement with DHA and should be administered under the supervision of a licensed medical practitioner.

DIRECTIONS FOR USE

One softgel daily, regardless of lactation status, or as prescribed by a licensed medical practitioner

STATEMENT OF IDENTITY

Supplement Facts
Serving Size: 1 Softgel
Amount Per Serving |  | % Daily Value for Pregnant and Lactating Women
Vitamin C (as ascorbic acid) | 100 mg | 83%
Vitamin D (Vitamin D3 as cholecalciferol) | 10 mcg (400 IU) | 67%
Vitamin E (as d-alpha tocopherol) | 20.1 mg (30 IU) | 106%
Thiamin (as thiamine mononitrate) | 3 mg | 214%
Riboflavin | 3 mg | 188%
Vitamin B6 (as pyridoxine HCl) | 20 mg | 1000%
Folate | 1700 mcg DFE (1 mg Folic Acid) | 283%
Vitamin B12 (as cyanocobalamin) | 15 mcg | 536%
Iron (as ferrous fumarate) | 28 mg | 104%
Magnesium (as magnesium oxide) | 30 mg | 8 %
Zinc (as zinc oxide) | 20 mg | 154%
Copper (as cupric sulfate) | 1 mg | 77%
Omega-3 Fatty Acids (DHA-EPA) | 200 mg | [Daily Value not established]

Other ingredients: Gelatin, Soybean Oil, Glycerin, Purified Water, Yellow Beeswax, Soy Lecithin, Titanium Dioxide, Ethyl Vanillin, FD&C Yellow #6, FD&C Red #40.

Contains: Fish and Soy

KEEP THIS OUT OF REACH OF CHILDREN

CONTRAINDICTIONS

WesNate DHA should not be used by patients with known history of hypersensitivity to any of its ingredients.

WARNING: Accidental overdose of iron-containing products is a leading cause of fatal poisoning in children under 6. KEEP THIS PRODUCT OUT OF REACH OF CHILDREN. In case of accidental overdose, call a doctor or poison control center immediately.

CAUTIONS

High levels of folic acid may, especially in older adults, hide signs of Vitamin B-12 deficiency (such as pernicious anemia, a condition that can cause nerve damage).

Concurrent use of folic acid has been associated with enhanced phenytoin metabolism, lowering the level of the AED in the blood and allowing breakthrough seizures to occur. Caution should be used when prescribing this product among patients who are receiving treatment with phenytoin or other anticonvulsants.

Exercise caution with the concomitant use of folinic acid and trimethoprim-sulfamethoxazole for the acute treatment of Pneumocystis carinii pneumonia in patients with HIV infection as it is associated with increased rates of treatment failure and mortality in a placebo controlled study.

The action of levodopa is antagonized by pyridoxine.

Products containing iron should not be used during dimercaprol therapy. Dimercaprol can bind to iron and cause kidney damage.

Avoid administering omega-3 fatty acids to patients with inherited or acquired predisposition toward bleeding, including patients taking anticoagulants. Exercise caution with these patients to ensure that the prescribed dosage of DHA does not exceed 1 gram (1000 mg) per day.

Side Effects

Allergic reactions have been reported following oral administration of folic acid.

Iron can cause mild gastrointestinal side effects, particularly when taken on an empty stomach.

DRUG INTERACTIONS

Folic Acid

Concurrent use of folic acid has been associated with enhanced phenytoin metabolism, lowering the level of the AED in the blood and allowing breakthrough seizures to occur.

Folinic acid may enhance the toxicity of fluorouracil.

High levels of folic acid may result in decreased serum levels of pyrimethamine.

Concurrent administration of chloramphenicol and folinic acid in folate-deficient patients may result in antagonism of the hematopoietic response to folate.

Antiepileptic drugs (including, but not limited to, phenytoin, carbamazepine, primidone, valproic acid, fosphenytoin, valproate, phenobarbital and lamotrigine) have been shown to impair folate absorption and increase the metabolism of circulating folate.

Fluoxetine

Fluoxetine exerts a noncompetitive inhibition of the 5-methyltetrahydrofolate active transport system in the intestine.

Decreased folic acid levels have been reported to be associated with the administration of Cholestyramine, Colestipol, Cycloserine, Dihydrofolate Reductase Inhibitors (aminopterin, methotrexate, pyrimethamine, triamterene, and trimethoprim), L-dopa, colchicine, oral contraceptives, methylprednisolone, pancreatic extracts (pancreatin, pancrelipase), prolonged intravenous pentamidine, smoking and alcohol consumption, sulfasalazine, metformin, heme iron, isotretinoin, and after a 6-month course of therapy, warfarin can produce a significant impairment of folate status.

Thiamin (Vitamin B1)

Furosemide, a loop diuretic, can decrease thiamin levels.

There have been case reports that fluorouracil may increase thiamin metabolism.

Vitamin B6

Vitamin B6 should not be given to patients receiving the drug levodopa because the action of levodopa is antagonized by Vitamin B6. However, Vitamin B6 may be used concurrently in patients receiving a preparation containing both carbidopa and levodopa.

Isoniazid can produce a Vitamin B6 deficiency.

Vitamin B12

Antibiotics, cholestyramine, colchicine, colestipol, metformin, para-aminosalicylic acid, and potassium chloride may decrease the absorption of vitamin B12 , and nitrous oxide can produce a functional vitamin B12 deficiency.

Vitamin D3

Some thiazide diuretics, such as hydrochlorothiazide, as well as antacids, bile acid sequestrants (such as cholestyramine), mineral oil, orlistat, olestra, cimetidine, and anticonvulsant medications may reduce the absorption or increase the catabolism of Vitamin D.

Vitamin D supplementation should not be given with calcium to patients with hypercalcemia or conditions that may lead to hypercalcemia such as hyperparathyroidism or those who form calcium-containing kidney stones.

Iron

Iron supplements might reduce the amounts of levodopa available to the body and diminish its clinical effectiveness.

Levothyroxine ingested simultaneously with iron can result in clinically significant reductions in levothyroxine efficacy.

Proton pump inhibitors reduce the acidity of stomach contents and can reduce iron absorption.

Zinc

Zinc may decrease absorption of quinolone or tetracycline antibiotics.

Cupric oxide

Concomitant use of penicillamine and copper can cause decreased absorption of both substances.

Omega-3 Fatty Acids

Ingestion of more than 3 grams per day of omega-3 fatty acids (ALA, EPA, and DHA) may have potential antithrombotic effects, and may increase bleeding times.

Avoid administering omega-3 fatty acids to patients with inherited or acquired predisposition toward bleeding, including patients taking anticoagulants. Exercise caution with these patients to ensure that the prescribed dosage of DHA does not exceed 1 gram (1000 mg) per day.

PREGNANT AND NURSING MOTHERS

WesNate DHA s a prescription folate dietary supplement formulated for use before, during and/ or after pregnancy regardless of lactation status.

HEALTH CLAIM

KEEP THIS PRODUCT OUT OF REACH OF CHILDREN.

HOW SUPPLIED

WesNate DHA is supplied as oval, orange colored softgel, imprinted with "317" dispensed in bottles of 30 softgels.

69367-317-30

STORAGE

Store at controlled room temperature 15° to 30°C (59° to 86°F).

Protect from light and moisture. Dispense in a tight, light-resistant container.

HEALTH CLAIM

Call your medical practitioner about side effects. You may report side effects by calling Westminster at 1-844-221-7294 or FDA at 1-800-FDA-1088.

HEALTH CLAIM

KEEP THIS AND ALL DRUGS OUT OF REACH OF CHILDREN

HEALTH CLAIM

Rx
Manufactured for:
Westminster Pharmaceuticals, LLC
Nashville, TN 37217
Rev. 03/25

PRINCIPAL DISPLAY PANEL - 30 Softgel Bottle Label

69367-317-30
Rx

WesNate DHA

PRENATAL/POSTNATAL

Prescription Dietary
Supplement with DHA

30 Softgels

Westminster
Pharmaceuticals